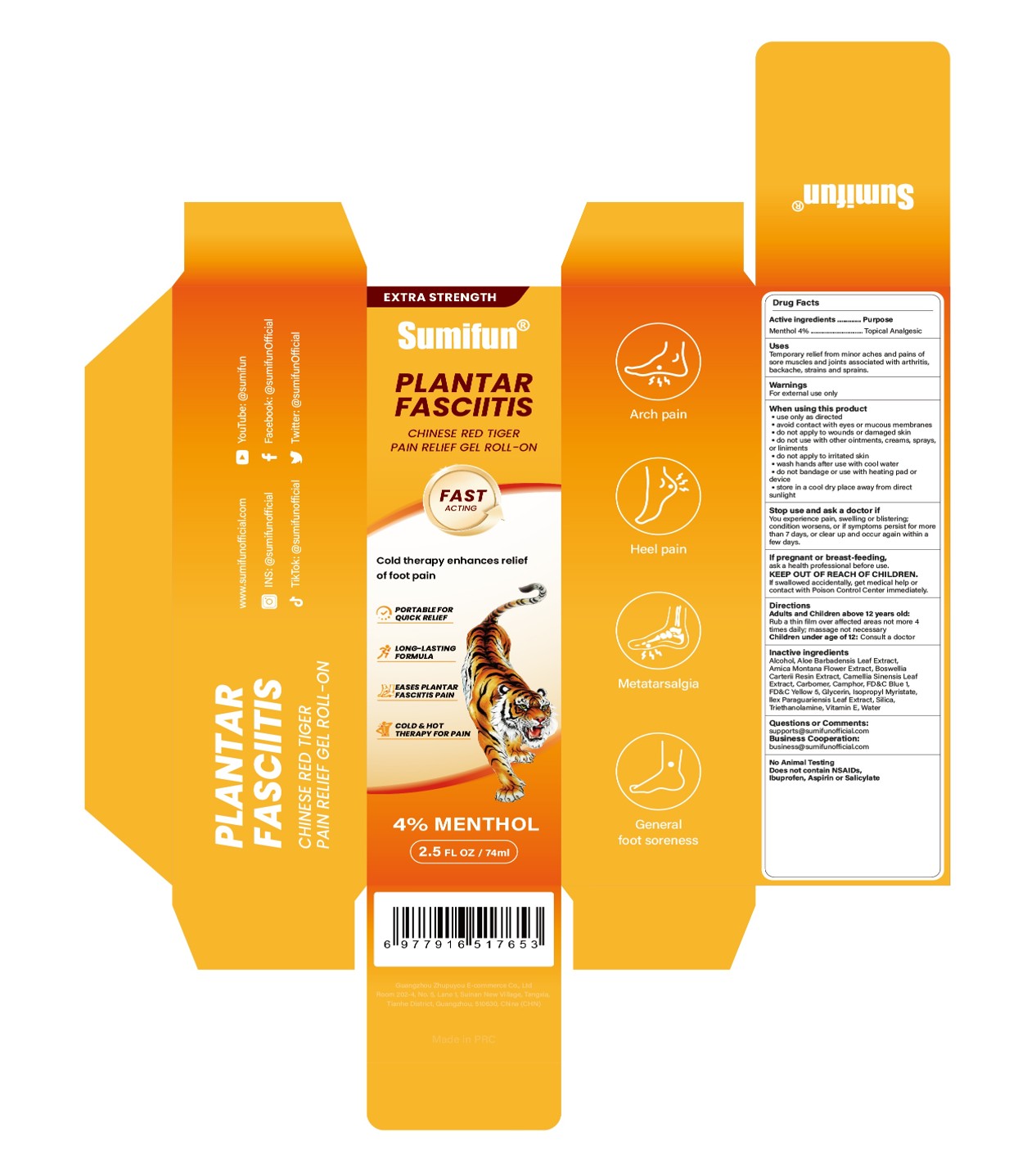 DRUG LABEL: Plantar Fasciitis  Chinese Red Tiger Pain Relief Gel Roll-On
NDC: 84165-009 | Form: GEL
Manufacturer: Guangzhou Zhupuyou E-commerce Co., Ltd
Category: otc | Type: HUMAN OTC DRUG LABEL
Date: 20250515

ACTIVE INGREDIENTS: MENTHOL 4 g/100 mL
INACTIVE INGREDIENTS: ILEX PARAGUARIENSIS LEAF; ISOPROPYL MYRISTATE; CAMPHOR (SYNTHETIC); CARBOMER; OLIBANUM; CAMELLIA SINENSIS LEAF; GLYCERIN; ALOE BARBADENSIS LEAF; ALCOHOL 95%; ARNICA MONTANA FLOWER; SILICA; WATER; TRIETHANOLAMINE; .ALPHA.-TOCOPHEROL, D-; FD&C BLUE NO. 1; FD&C YELLOW NO. 5

84165-009 Plantar Fasciitis Chinese Red Tiger Pain Relief Gel Roll-On

ACTIVE INGREDIENT

Menthol 4%

PURPOSE

Topical Analgesic

INDICATIONS AND USAGE

Temporary relief from minor aches and pains ofsore muscles and joints associated with arthritis,backache, strains and sprains.

WARNINGS

For external use only

do not apply to wounds or damaged skin.
do not use with other ointments, creams, sprays,or liniments
do not apply to irritated skin.
do not bandage or use with heating pad ordewice.

WHEN USING

use only as directed
avoid contact with eyes or mucous membranes.
wash hands after use with cool water.

STOP USE

You experience pain, swelling or blistering;condition worsens, or if symptoms persist for morethan 7 days, or clear up and occur again within afew days.

KEEP OUT OF REACH OF CHILDREN

If swallowed accidentally, get medical help orcontact with Poison Control Center immediately,

DOSAGE AND ADMINISTRATION

Aduits and Children above 12 years old:
Rub a thin film over affected areas not more 4times daily, massage not necessary
Children under age of 12: Consult a doctor

INACTIVE INGREDIENT

Alcohol
Aloe barbadensis leaf extract
Arnica montana flower extract
Boswellia carterii resin extract
Camellia sinensis leaf extract
Carbomer
Camphor
FD&C Blue 1
FD&C Yellow 5
Glycerin
Ilex Paraguariensis Leaf Extract
Isopropyl Myristate
Silica
Triethanolamine
Vitamin E
Water